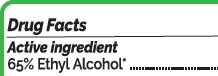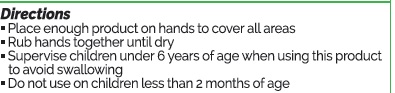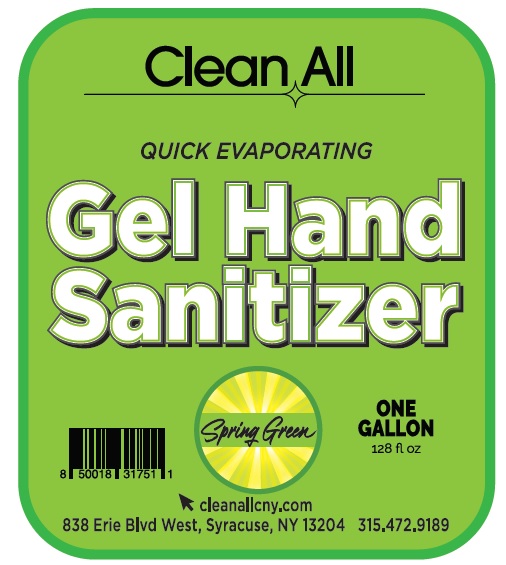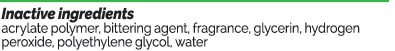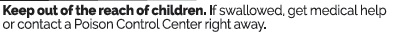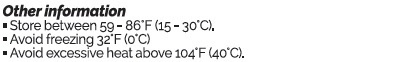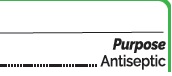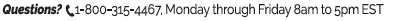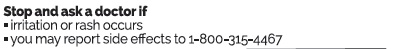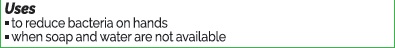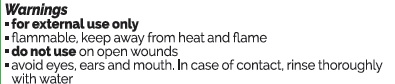 DRUG LABEL: Spring Green Gel Hand Sanitizer
NDC: 75660-144 | Form: GEL
Manufacturer: Solvents and Petroleum
Category: otc | Type: HUMAN OTC DRUG LABEL
Date: 20201014

ACTIVE INGREDIENTS: ALCOHOL 65 mL/100 mL
INACTIVE INGREDIENTS: GLYCERIN 1.35 mL/100 mL; HYDROGEN PEROXIDE 0.18 mL/100 mL; WATER 30.95 mL/100 mL; POLYETHYLENE GLYCOL, UNSPECIFIED 2 mL/100 mL; ACRYLATES/VINYL ISODECANOATE CROSSPOLYMER (10000 MPA.S NEUTRALIZED AT 0.5%) 0.5 mL/100 mL; DENATONIUM BENZOATE 0.01 mL/100 mL; FRAGRANCE FLORAL ORC0902236 0.01 mL/100 mL

Spring Green Scented Clean All Gel Hand Sanitizer

Active Ingredient(s)

Alcohol 65%

Purpose

Antiseptic, Hand Sanitizer

Use

to reduce bacteria on hands. For use when soap and water are not available.

Warnings

For external use only. Flammable. Keep away from heat or flame. do not use on open wounds. void eyes, ears and mouth. In case of contact rinse thoroughly.

Stop use and ask a doctor if irritation or rash occurs. These may be signs of a serious condition. You may report side effects to 1-800-315-4467

Keep out of reach of children. If swallowed, get medical help or contact a Poison Control Center right away.

Directions

- Place enough product on hands to cover all surfaces. Rub hands together until dry.
- Supervise children under 6 years of age when using this product to avoid swallowing.
- do not use on children less than 2 months in age

Other information

- Store between 15-30C (59-86F)
- Avoid freezing and excessive heat above 40C (104F)

Inactive ingredients

acrylate polymer, bittering agent, fragrance, glycerin, hydrogen peroxide, polyethylene glycol, water

Questions

1-800-315-4467 Monday through riday 8am - 5pm